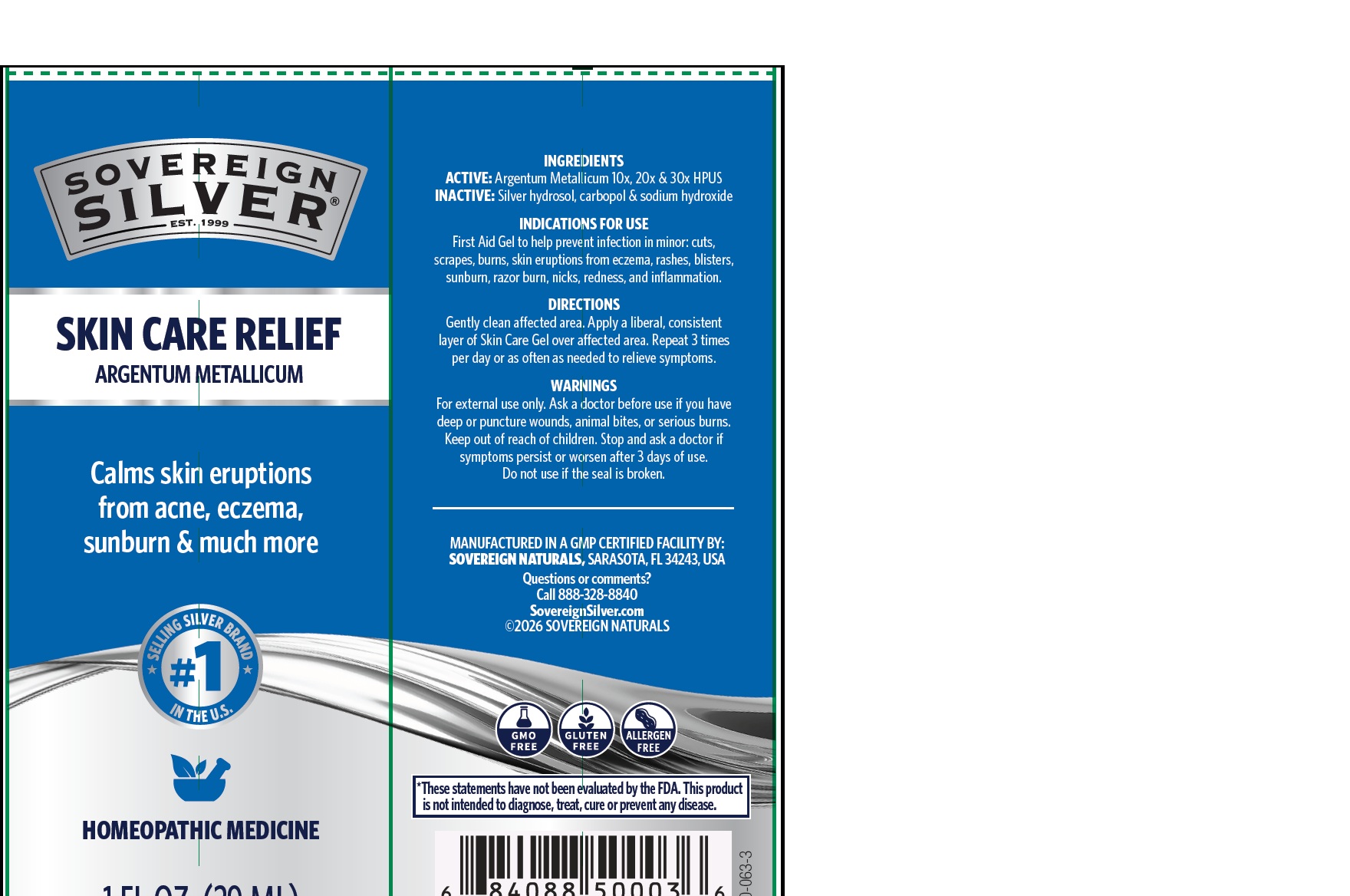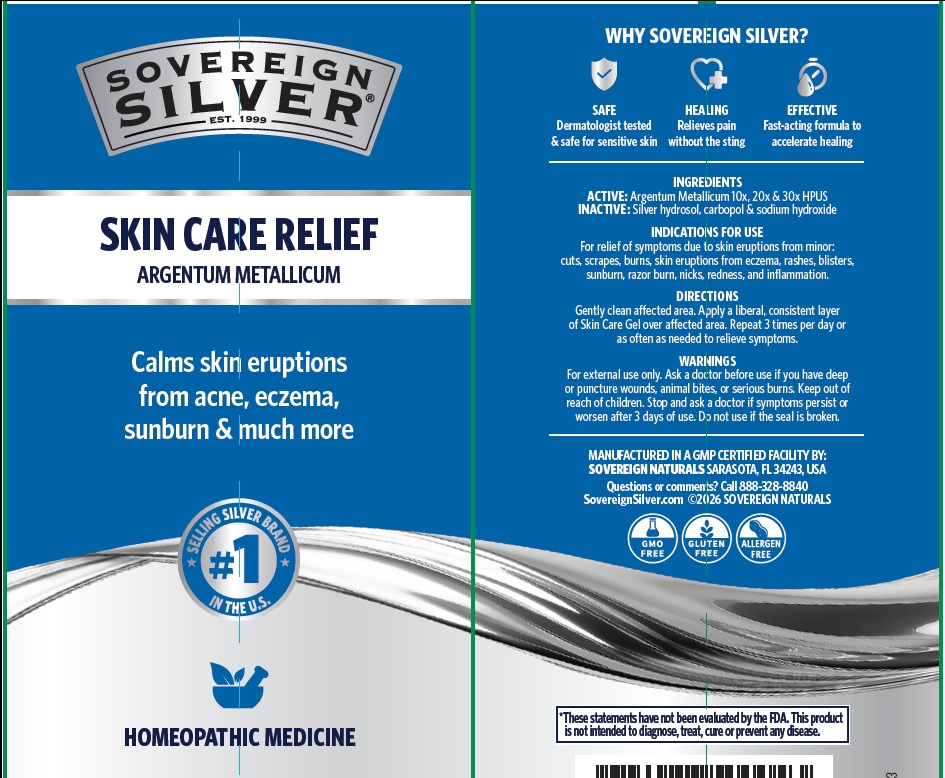 DRUG LABEL: Sovereign Silver

NDC: 52166-015 | Form: GEL
Manufacturer: Natural Immunogenics Corp.dba SOVEREIGN NATURALS
Category: homeopathic | Type: HUMAN OTC DRUG LABEL
Date: 20251124

ACTIVE INGREDIENTS: SILVER 30 [hp_X]/1 mL
INACTIVE INGREDIENTS: CARBOMER HOMOPOLYMER TYPE B (ALLYL PENTAERYTHRITOL CROSSLINKED); SODIUM HYDROXIDE

Homeopathic Drug

ACTIVE INGREDIENT

Ingredients

ACTIVE: Argentum Metallicum 10x, 20x and 30x HPUS

INACTIVE

Silver hydrosol,carbopol and sodium hydroxide

Purpose

Natural healing gel skin care

Keep out of reach of children.

Warnings

For external use only. Ask a doctor before use if you have deep or puncture wounds, animal bites or serious burns.

ASK DOCTOR

Stop and ask a doctor if symptoms persist or worsen after 3 days of use. Do not use if seal is broken

Directions

Gently clean affected area. Apply a liberal, consistent layer of Skin Care Gel over affected area. Repeat 3 times per day or as often as needed to relieve symptoms. Safe on sensitive skin.

Indications for Use

For relief of symptoms due to skin eruptions from acne, eczema, minor infection, rashes, blisters -Sunburn – Razor Burn – minor nicks & cuts – redness – minor inflammation